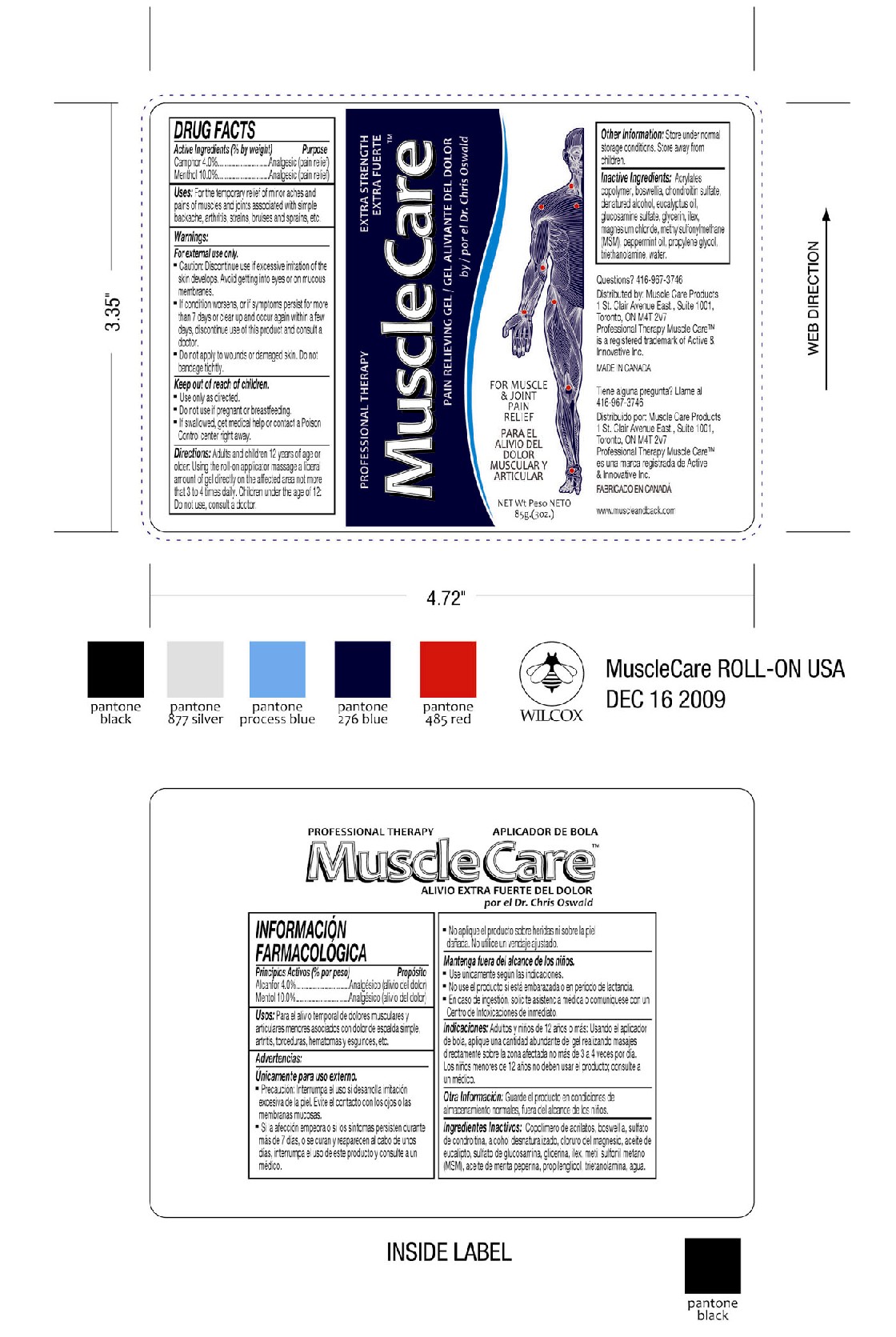 DRUG LABEL: Professional Therapy Muscle Care Pain Relieving Gel by Dr. Chris Oswald
NDC: 49795-416 | Form: GEL
Manufacturer: Nutri-Dyn Products Ltd. dba Professional Health Products
Category: otc | Type: HUMAN OTC DRUG LABEL
Date: 20100118

ACTIVE INGREDIENTS: Menthol 10 g/100 g; Camphor 4 g/100 g
INACTIVE INGREDIENTS: Water; Eucalyptus oil; Peppermint oil; Propylene glycol; Glycerin; Dimethyl sulfone; Glucosamine sulfate; Magnesium chloride

Professional Therapy MuscleCare Pain Relieving Gel

DOSAGE AND ADMINISTRATION

Adults and children 12 years of age or older: Using the roll-on applicator massage a liberal amount of gel directly on the affected area not more than 3 to 4 times daily.
Children under the age of 12: Do not use, consult a doctor.

PACKAGE LABEL

PROFESSIONAL THERAPY MAXIMUM STRENGTH

MUSCLECARE

PAIN RELIEVING GEL by Dr. Chris Oswald

FOR MUSCLE AND JOINT PAIN RELIEF.
NET Wt. 85g (3oz)

Warnings:

For external use only.

CAUTION:

- Discontinue use if excessive irritation of the skin develops.
- Avoid getting into eyes or on mucous membranes.
- If condition worsens, or if symptoms persist for more than 7 days or clear up and occur again within a few days, discontinue use of this product and consult a doctor.
- Do not apply to wounds or damaged skin. Do not bandage tightly.

ACTIVE INGREDIENT

Active Ingredients (% by weight) Purpose Active Ingredients (% by weight) Purpose

Camphor 4.0 %.............Analgelsic (pain relief) Menthol 10.0 %.............Analgelsic (pain relief)

INACTIVE INGREDIENT

Acrylates, copolymer, boswellia, chondroitin sulfate, denatured alcohol, eucalyptus oil, glucosamine sulfate, glycerin, ilex, magnesium chloride, methylsulfonylmethane (MSM), peppermint oil, propylene glycol, triethanolamine, water.

DESCRIPTION

For the temporary relief of minor aches and pains of muscles and joints associated with simple backache, arthritis, strains, bruises and sprains, etc.

Keep out of reach of children.

- Use only as directed.
- Do not use if pregnant or breastfeeding.
- If swallowed, get medical help or contact a Poison Control center right away.

STORAGE AND HANDLING

Store under normal storage conditions. Store away from children

REFERENCES

Questions? 416-967-3746 MADE IN CANADA

Manufactured for / ergo-health a division of Active and Innovative Inc.

1 St. Clair Avenue East, Suite 1001, Toronto ON M4T 2V7 ergo-health and Muscle Care are registered trademarks of ergo-health, a division of Active and Innovative Inc. www.ergo-health.com